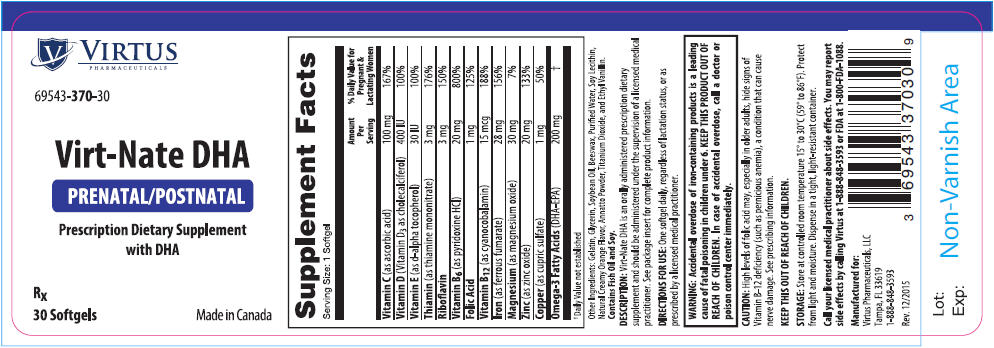 DRUG LABEL: Virt-Nate DHA
NDC: 69543-370 | Form: CAPSULE
Manufacturer: Virtus Pharmaceuticals
Category: other | Type: DIETARY SUPPLEMENT
Date: 20160121

ACTIVE INGREDIENTS: ASCORBIC ACID 100 mg/1 1; CHOLECALCIFEROL 400 [iU]/1 1; .ALPHA.-TOCOPHEROL, D- 30 [iU]/1 1; THIAMINE MONONITRATE 3 mg/1 1; RIBOFLAVIN 3 mg/1 1; PYRIDOXINE HYDROCHLORIDE 20 mg/1 1; FOLIC ACID 1 mg/1 1; CYANOCOBALAMIN 15 ug/1 1; FERROUS FUMARATE 28 mg/1 1; MAGNESIUM OXIDE 30 mg/1 1; ZINC OXIDE 20 mg/1 1; CUPRIC SULFATE 1 mg/1 1; OMEGA-3 FATTY ACIDS 200 mg/1 1
INACTIVE INGREDIENTS: GELATIN; GLYCERIN; SOYBEAN OIL; YELLOW WAX; WATER; LECITHIN, SOYBEAN; TITANIUM DIOXIDE; ETHYL VANILLIN

Virt-Nate DHA

STATEMENT OF IDENTITY

Prenatal/Postnatal Prescription Dietary Supplement

69543-370-30

Rx

DESCRIPTION

Virt-Nate DHA is an orally administered prenatal/postnatal prescription dietary supplement with DHA and should be administered under the supervision of a licensed medical practitioner.

DIRECTIONS FOR USE

Before, during, and/or after pregnancy regardless of lactation status, one softgel daily or as directed by a licensed healthcare practitioner.

Supplement Facts
Serving Size: 1 Softgel
 | Amount Per Serving | % Daily Value for Pregnant & Lactating Women
Vitamin C (as ascorbic acid) | 100 mg | 167%
Vitamin D (Vitamin D3 as cholecalciferol) | 400 IU | 100%
Vitamin E (as d-alpha tocopherol) | 30 IU | 100%
Thiamin (as thiamine mononitrate) | 3 mg | 176%
Riboflavin | 3 mg | 150%
Vitamin B6 (as pyridoxine HCl) | 20 mg | 800%
Folic Acid | 1 mg | 125%
Vitamin B12 (as cyanocobalamin) | 15 mcg | 188%
Iron (as ferrous fumarate) | 28 mg | 156%
Magnesium (as magnesium oxide) | 30 mg | 7%
Zinc (as zinc oxide) | 20 mg | 133%
Copper (as cupric sulfate) | 1 mg | 50%
Omega-3 Fatty Acids (DHA-EPA) | 200 mg | [Daily Value not established]

Other Ingredients: Gelatin, Glycerin, Soybean Oil, Beeswax, Purified Water, Soy Lecithin, Natural Creamy Orange Flavor, Annatto Powder, Titanium Dioxide, and Ethyl Vanillin. Contains Fish Oil and Soy.

KEEP THIS OUT OF REACH OF CHILDREN

CONTRAINDICATIONS

Virt-Nate DHA should not be used by patients with known history of hypersensitivity to any of its ingredients.

WARNINGS

WARNING: Accidental overdose of iron-containing products is a leading cause of fatal poisoning in children under 6. KEEP THIS PRODUCT OUT OF REACH OF CHILDREN. In case of accidental overdose, call a doctor or poison control center immediately.

CAUTIONS

High levels of folic acid may, especially in older adults, hide signs of Vitamin B-12 deficiency (such as pernicious anemia, a condition that can cause nerve damage).

Concurrent use of folic acid has been associated with enhanced phenytoin metabolism, lowering the level of the AED in the blood and allowing breakthrough seizures to occur. Caution should be used when prescribing this product among patients who are receiving treatment with phenytoin or other anticonvulsants.

Exercise caution with the concomitant use of folinic acid and trimethoprim-sulfamethoxazole for the acute treatment of Pneumocystis carinii pneumonia in patients with HIV infection as it is associated with increased rates of treatment failure and mortality in a placebo controlled study.

The action of levodopa is antagonized by pyridoxine.

Products containing iron should not be used during dimercaprol therapy. Dimercaprol can bind to iron and cause kidney damage.

Avoid administering omega-3 fatty acids to patients with inherited or acquired predisposition toward bleeding, including patients taking anticoagulants. Exercise caution with these patients to ensure that the prescribed dosage of DHA does not exceed 1 gram (1000 mg) per day.

SIDE EFFECTS

Allergic sensitization has been reported following oral administration of folic acid.

Iron can cause mild gastrointestinal side effects, particularly when taken on an empty stomach.

DRUG INTERACTIONS

Folic Acid

Concurrent use of folic acid has been associated with enhanced phenytoin metabolism, lowering the level of the AED in the blood and allowing breakthrough seizures to occur.

Folinic acid may enhance the toxicity of fluorouracil.

High levels of folic acid may result in decreased serum levels of pyrimethamine.

Concurrent administration of chloramphenicol and folinic acid in folate-deficient patients may result in antagonism of the hematopoietic response to folate.

Antiepileptic drugs (including, but not limited to, phenytoin, carbamazepine, primidone, valproic acid, fosphenytoin, valproate, phenobarbital and lamotrigine) have been shown to impair folate absorption and increase the metabolism of circulating folate.

Fluoxetine

Fluoxetine exerts a noncompetitive inhibition of the 5-methyltetrahydrofolate active transport system in the intestine.

Decreased folic acid levels have been reported to be associated with the administration of Cholestyramine, Colestipol, Cycloserine, Dihydrofolate Reductase Inhibitors (aminopterin, methotrexate, pyrimethamine, triamterene, and trimethoprim), L-dopa, colchicine, oral contraceptives, methylprednisolone, pancreatic extracts (pancreatin, pancrelipase), prolonged intravenous pentamidine, smoking and alcohol consumption, sulfasalazine, metformin, heme iron, isotretinoin, and after a 6-month course of therapy, warfarin can produce a significant impairment of folate status.

Thiamin (Vitamin B1)

Furosemide, a loop diuretic, can decrease thiamin levels.

There have been case reports that fluorouracil may increase thiamin metabolism.

Vitamin B6

Vitamin B6 should not be given to patients receiving the drug levodopa because the action of levodopa is antagonized by Vitamin B6. However, Vitamin B6 may be used concurrently in patients receiving a preparation containing both carbidopa and levodopa.

Isoniazid can produce a Vitamin B6 deficiency.

Vitamin B12

Antibiotics, cholestyramine, colchicine, colestipol, metformin, para-aminosalicylic acid, and potassium chloride may decrease the absorption of vitamin B12, and nitrous oxide can produce a functional vitamin B12 deficiency.

Vitamin D3

Some thiazide diuretics, such as hydrochlorothiazide, as well as antacids, bile acid sequestrants (such as cholestyramine), mineral oil, orlistat, olestra, cimetidine, and anticonvulsant medications may reduce the absorption or increase the catabolism of Vitamin D.

Vitamin D supplementation should not be given with calcium to patients with hypercalcemia or conditions that may lead to hypercalcemia such as hyperparathyroidism or those who form calcium-containing kidney stones.

Iron

Iron supplements might reduce the amounts of levodopa available to the body and diminish its clinical effectiveness.

Levothyroxine ingested simultaneously with iron can result in clinically significant reductions in levothyroxine efficacy.

Proton pump inhibitors reduce the acidity of stomach contents and can reduce iron absorption.

Zinc

Zinc may decrease absorption of quinolone or tetracycline antibiotics.

Cupric oxide

Concomitant use of penicillamine and copper can cause decreased absorption of both substances.

Omega-3 Fatty Acids

Ingestion of more than 3 grams per day of omega-3 fatty acids (ALA, EPA, and DHA) may have potential antithrombotic effects, and may increase bleeding times.

Avoid administering omega-3 fatty acids to patients with inherited or acquired predisposition toward bleeding, including patients taking anticoagulants. Exercise caution with these patients to ensure that the prescribed dosage of DHA does not exceed 1 gram (1000 mg) per day.

PREGNANT AND NURSING MOTHERS

Virt-Nate DHA is a prescription folate dietary supplement formulated for use before, during and/or after pregnancy regardless of lactation status.

KEEP THIS PRODUCT OUT OF REACH OF CHILDREN.

HEALTH CLAIM

Adequate folate in healthful diets may reduce a woman's risk of having a child with a brain or spinal cord defect.

HOW SUPPLIED

Virt-Nate DHA is supplied as annatto colored softgel, imprinted with "V370," dispensed in bottles of 30 softgels.

STORAGE

Store at controlled room temperature 15° to 30°C (59° to 86°F).

Protect from light and moisture. Dispense in a tight, light-resistant container.

Call your licensed medical practitioner about side effects. You may report side effects by calling Virtus at 1-888-848-3593 or FDA at 1-800-FDA-1088.

KEEP THIS AND ALL DRUGS OUT OF THE REACH OF CHILDREN

Rx

Manufactured for
Virtus Pharmaceuticals, LLC
Tampa, FL 33619
1-888-848-3593

Made in Canada
Rev. 12/2015

PRINCIPAL DISPLAY PANEL - 30 Softgel Bottle Label

VIRTUS
PHARMACEUTICALS

69543-370-30

Virt-Nate DHA

PRENATAL/POSTNATAL

Prescription Dietary Supplement
with DHA

Rx
30 Softgels

Made in Canada